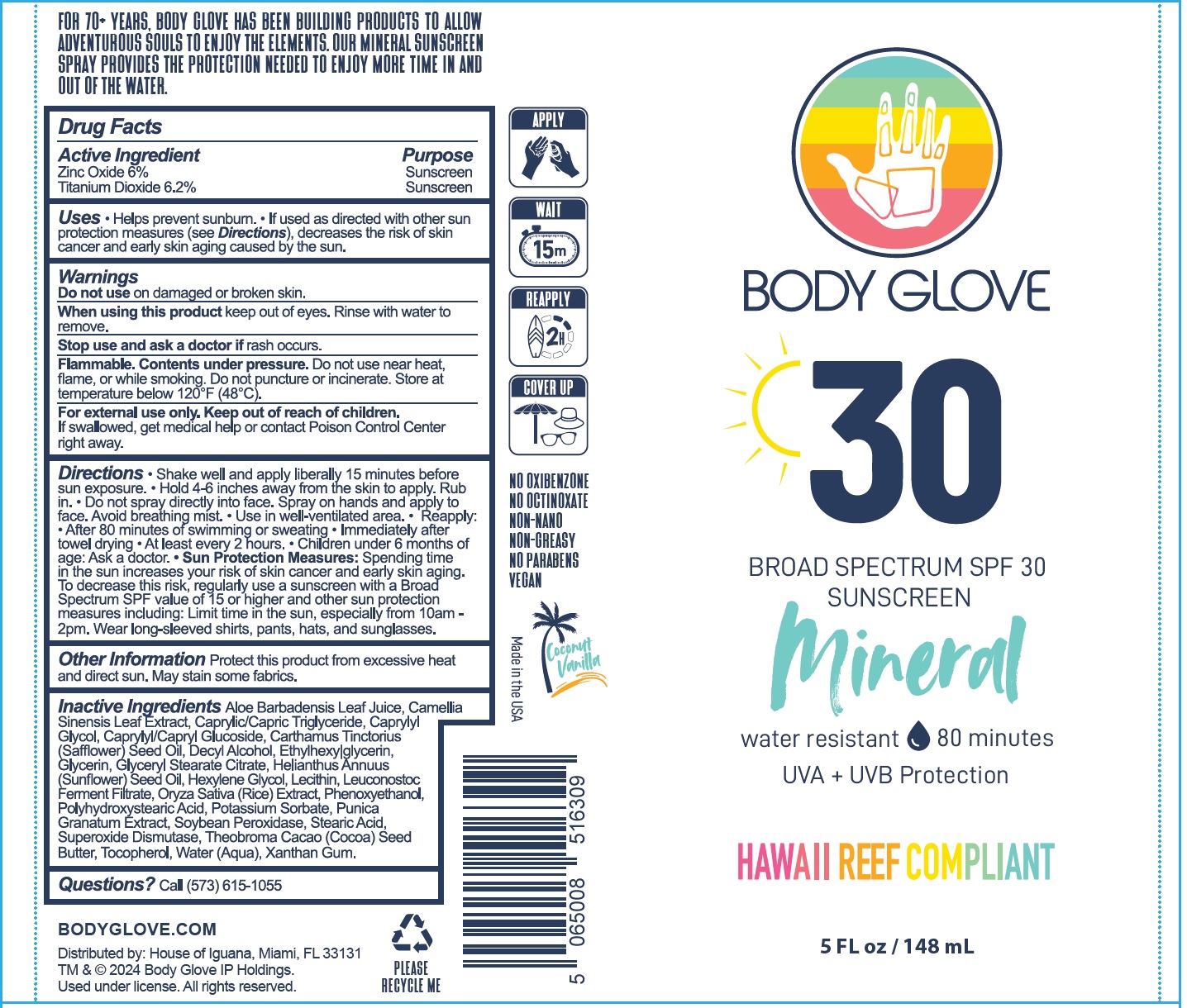 DRUG LABEL: Body Glove Sunscreen SPF 30
NDC: 85763-614 | Form: LIQUID
Manufacturer: SCUBASCREEN LLC
Category: otc | Type: HUMAN OTC DRUG LABEL
Date: 20250605

ACTIVE INGREDIENTS: ZINC OXIDE 60 mg/1 mL; TITANIUM DIOXIDE 62 mg/1 mL
INACTIVE INGREDIENTS: ALOE VERA LEAF JUICE; GREEN TEA LEAF; MEDIUM-CHAIN TRIGLYCERIDES; CAPRYLYL GLYCOL; CAPRYLYL/CAPRYL OLIGOGLUCOSIDE; SAFFLOWER OIL; DECYL ALCOHOL; ETHYLHEXYLGLYCERIN; GLYCERIN; GLYCERYL STEARATE CITRATE; SUNFLOWER OIL; HEXYLENE GLYCOL; RICE GERM; PHENOXYETHANOL; POTASSIUM SORBATE; PUNICA GRANATUM ROOT BARK; STEARIC ACID; SUPEROXIDE DISMUTASE (SACCHAROMYCES CEREVISIAE); COCOA BUTTER; TOCOPHEROL; WATER; XANTHAN GUM

Body Glove Sunscreen SPF 30

Active Ingredient

Zinc Oxide 6%
Titanium Dioxide 6.2%

Purpose

Sunscreen

Uses:

- Helps prevent sunburn.
- If used as directed with other sun protection measures (see Directions), decreases the risk of skin cancer and early skin aging caused by the sun.

Warnings

Flammable. Contents under pressure.Do not use near heat, flame, or while smoking. Do not puncture or incinerate. Store at temperature below 120º F (48ºC).
For external use only.

Do not use

on damaged or broken skin.

When using this product

keep out of eyes. Rinse with water to remove.

Stop use and ask a doctor if

rash occurs.

Keep out of reach of children.

If swallowed, get medical help or contact a Poison Control Center right away.

Directions:

- Shake well and apply liberally 15 minutes before sun exposure.
- Hold 4-6 inches away from the skin to apply. Rub in.
- Do not spray directly into face. Spray on hands and apply to face. Avoid breathing mist.
- Use in well-ventilated area.
- Reapply:
- After 80 minutes of swimming or sweating
- Immediately after towel drying
- At least every 2 hours.
- Children under 6-months of age: Ask a doctor.
- Sun Protection Measures:Spending time in the sun increases your risk of skin cancer and early skin aging. To decrease the risk, regularly use a sunscreen with Broad Spectrum SPF of 15 or higher and other sun protection measures including: Limit time in the sun, especially from 10 am. - 2 pm. Wear long-sleeved shirts, pants, hats, and sunglasses.

Other Information

- Protect this product from excessive heat and direct sun. May stain some fabrics.

Inactive Ingredients:

Aloe Barbadensis Leaf Juice, Camellia Sinensis Leaf Extract, Caprylic/Capric Triglyceride, Caprylyl Glycol, Caprylyl/Capryl Glucoside, Carthamus Tinctorious (Safflower) Seed Oil, Decyl Alcohol, Ethylhexylglycerin, Glycerin, Glyceryl Stearate Citrate, Helianthus Annuus (Sunflower) Seed Oil, Hexylene Glycol, Lecithin, Leuconostoc Ferment Filtrate, Oryza Sativa (Rice) Extract, Phenoxyethanol, Polyhydroxystearic Acid, Potassium Sorbate, Punica Granatum Extract, Soybean Peroxidase, Stearic Acid, Superoxide Dismutase, Theobroma Cacao (Cocoa) Seed Butter, Tocopherol, Water (Aqua), Xanthan Gum

Questions?

Call (573) 615-1055